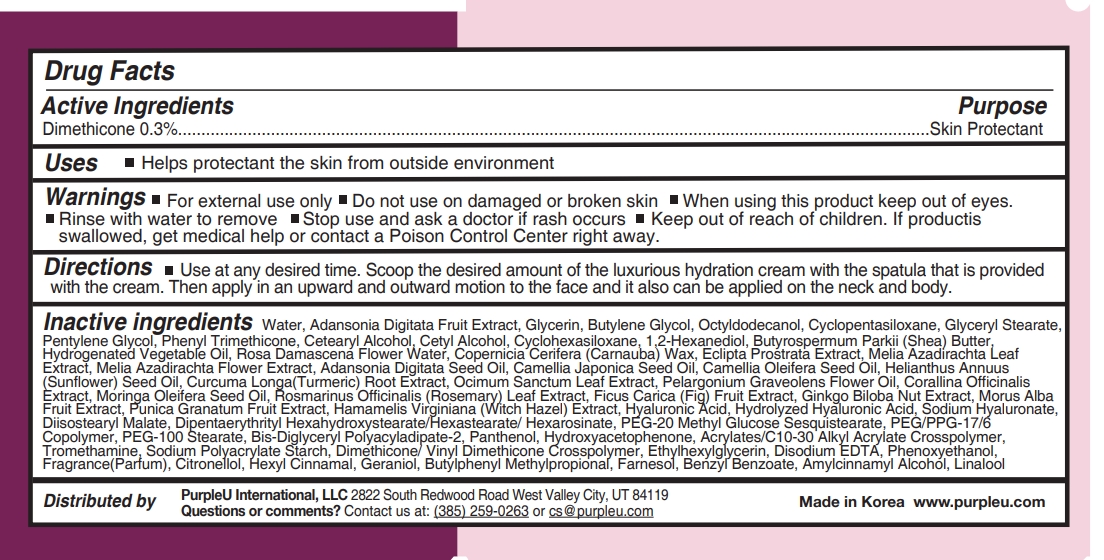 DRUG LABEL: PurpleU BAOBAB AND ROSE DEEP HYDRATION Cream THERAPY
NDC: 90069-201 | Form: CREAM
Manufacturer: Purple U Co., Ltd
Category: otc | Type: HUMAN OTC DRUG LABEL
Date: 20200902

ACTIVE INGREDIENTS: DIMETHICONE 0.3 g/100 mL
INACTIVE INGREDIENTS: CAMELLIA JAPONICA SEED OIL; DIPENTAERYTHRITYL HEXAHYDROXYSTEARATE; PEG-20 METHYL GLUCOSE SESQUISTEARATE; BIS-DIGLYCERYL POLYACYLADIPATE-2; PANTHENOL; HYDROXYACETOPHENONE; AZADIRACHTA INDICA LEAF; ETHYLHEXYLGLYCERIN; EDETATE DISODIUM ANHYDROUS; PHENOXYETHANOL; BUTYLPHENYL METHYLPROPIONAL; FARNESOL; AZADIRACHTA INDICA FLOWER; ADANSONIA DIGITATA SEED OIL; SUNFLOWER OIL; HOLY BASIL LEAF; GINKGO BILOBA SEED; DIISOSTEARYL MALATE; PEG/PPG-17/6 COPOLYMER; PEG-100 STEARATE; WATER; GLYCERIN; GLYCERYL MONOSTEARATE; PENTYLENE GLYCOL; PHENYL TRIMETHICONE; CETOSTEARYL ALCOHOL; 1,2-HEXANEDIOL; CAMELLIA OIL; TURMERIC; ROSEMARY; WHITE MULBERRY; HAMAMELIS VIRGINIANA TOP; HYALURONIC ACID; HYALURONATE SODIUM; DIPENTAERYTHRITYL HEXASTEARATE; ADANSONIA DIGITATA FRUIT; BUTYLENE GLYCOL; OCTYLDODECANOL; CYCLOMETHICONE 5; CETYL ALCOHOL; CYCLOMETHICONE 6; SHEA BUTTER; ECLIPTA PROSTRATA LEAF; .ALPHA.-AMYLCINNAMYL ALCOHOL; PELARGONIUM GRAVEOLENS FLOWER OIL; CORALLINA OFFICINALIS; MORINGA OLEIFERA SEED OIL; FIG; POMEGRANATE; CARBOMER INTERPOLYMER TYPE A (ALLYL SUCROSE CROSSLINKED); TROMETHAMINE; .BETA.-CITRONELLOL, (R)-; .ALPHA.-HEXYLCINNAMALDEHYDE; GERANIOL; BENZYL BENZOATE; LINALOOL, (+/-)-; ROSA DAMASCENA FLOWER OIL; CARNAUBA WAX

90069-201

Active Ingredients

Dimethicone 0.3%

Purpose

Skin Protectant

Uses

Helps protectant the skin from outside environment

Warnings

For external use only

Do not use on damaged or broken skin

When using this product keep out of eyes

Rinse with water to remove

Warnings

Stop use and ask a doctor if rash occurs

Warnings

Keep out of reach of children. If productis swallowed, get medical help or contact a Poison Control Center right away.

Directions

Use at any desired time. Scoop the desired amount of the luxurious hydration cream with the spatula that is provided with the cream. Then apply in an upward and outward motion to the face and it also can be applied on the neck and body.

Inactive ingredients

Water, Adansonia Digitata Fruit Extract, Glycerin, Butylene Glycol, Octyldodecanol, Cyclopentasiloxane, Glyceryl Stearate, Pentylene Glycol, Phenyl Trimethicone, Cetearyl Alcohol, Cetyl Alcohol, Cyclohexasiloxane, 1,2-Hexanediol, Butyrospermum Parkii (Shea) Butter, Hydrogenated Vegetable Oil, Rosa Damascena Flower Water, Copernicia Cerifera (Carnauba) Wax, Eclipta Prostrata Extract, Melia Azadirachta Leaf Extract, Melia Azadirachta Flower Extract, Adansonia Digitata Seed Oil, Camellia Japonica Seed Oil, Camellia Oleifera Seed Oil, Helianthus Annuus (Sunflower) Seed Oil, Curcuma Longa(Turmeric) Root Extract, Ocimum Sanctum Leaf Extract, Pelargonium Graveolens Flower Oil, Corallina Officinalis Extract, Moringa Oleifera Seed Oil, Rosmarinus Officinalis (Rosemary) Leaf Extract, Ficus Carica (Fig) Fruit Extract, Ginkgo Biloba Nut Extract, Morus Alba Fruit Extract, Punica Granatum Fruit Extract, Hamamelis Virginiana (Witch Hazel) Extract, Hyaluronic Acid, Hydrolyzed Hyaluronic Acid, Sodium Hyaluronate, Diisostearyl Malate, Dipentaerythrityl Hexahydroxystearate/Hexastearate/ Hexarosinate, PEG-20 Methyl Glucose Sesquistearate, PEG/PPG-17/6 Copolymer, PEG-100 Stearate, Bis-Diglyceryl Polyacyladipate-2, Panthenol, Hydroxyacetophenone, Acrylates/C10-30 Alkyl Acrylate Crosspolymer, Tromethamine, Sodium Polyacrylate Starch, Dimethicone/ Vinyl Dimethicone Crosspolymer, Ethylhexylglycerin, Disodium EDTA, Phenoxyethanol, Fragrance(Parfum), Citronellol, Hexyl Cinnamal, Geraniol, Butylphenyl Methylpropional, Farnesol, Benzyl Benzoate, Amylcinnamyl Alcohol, Linalool